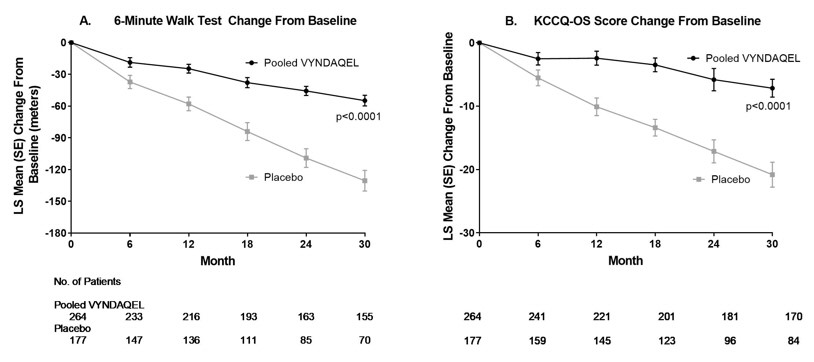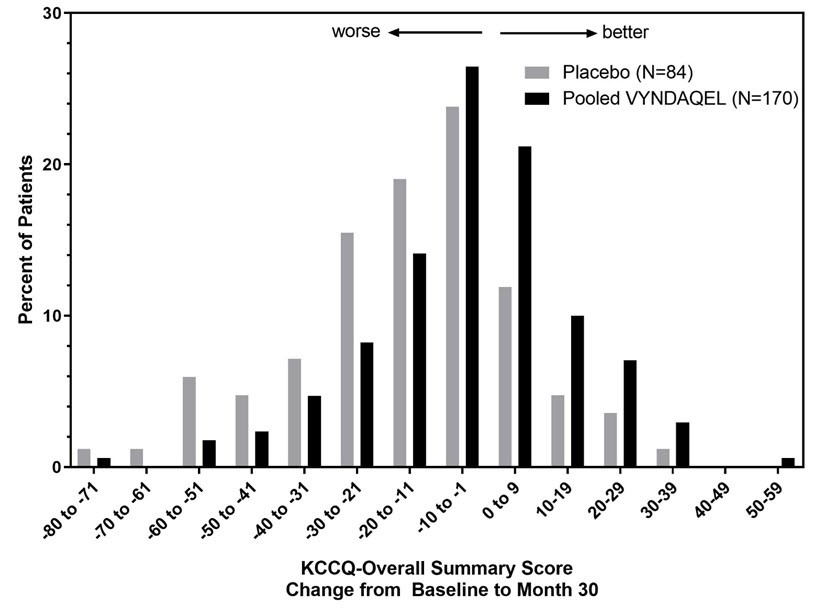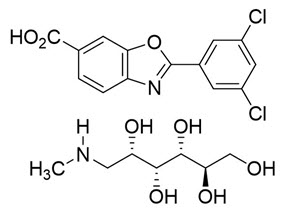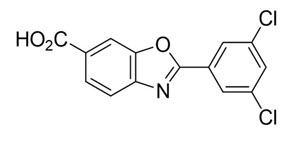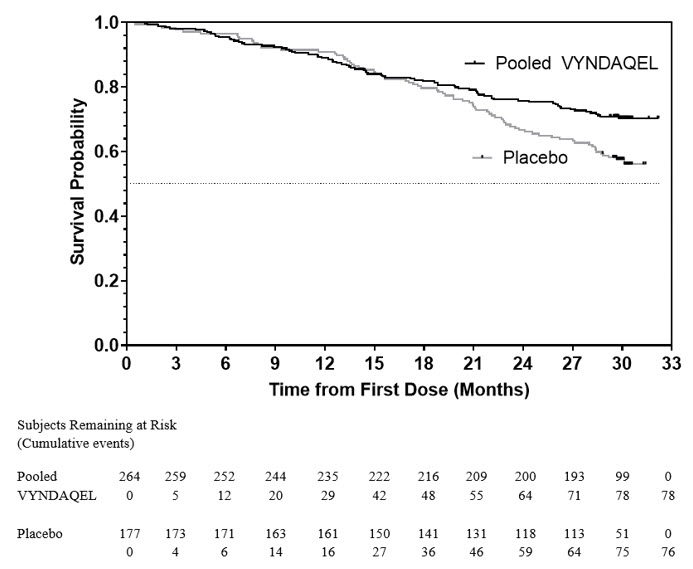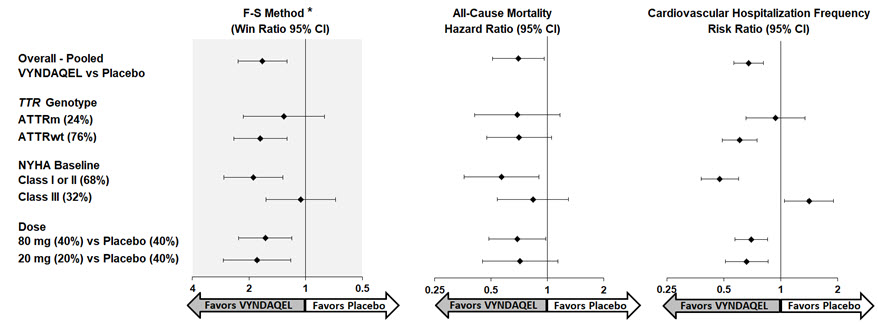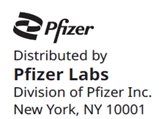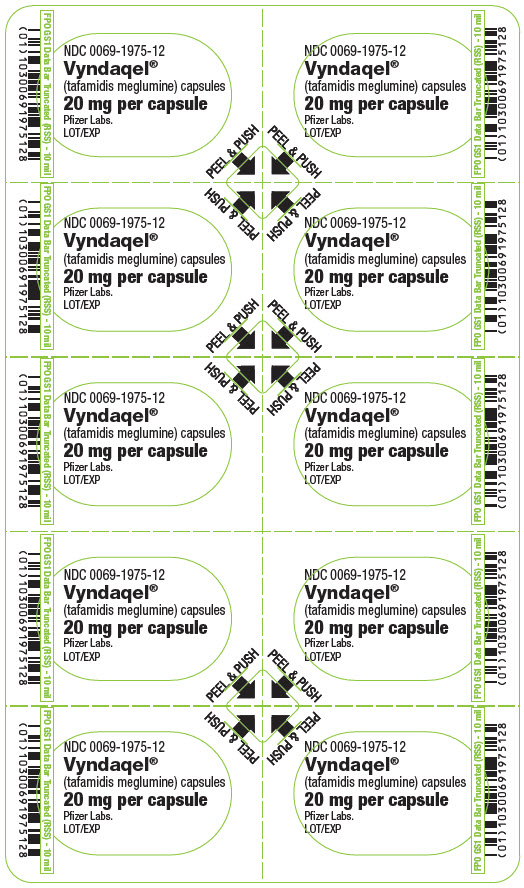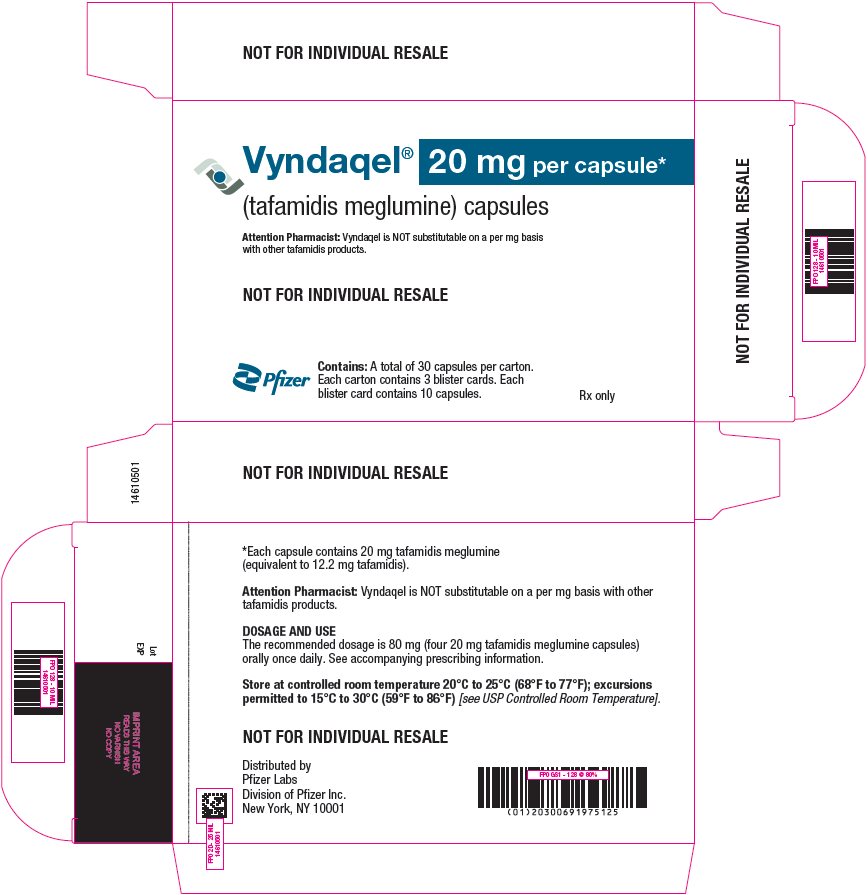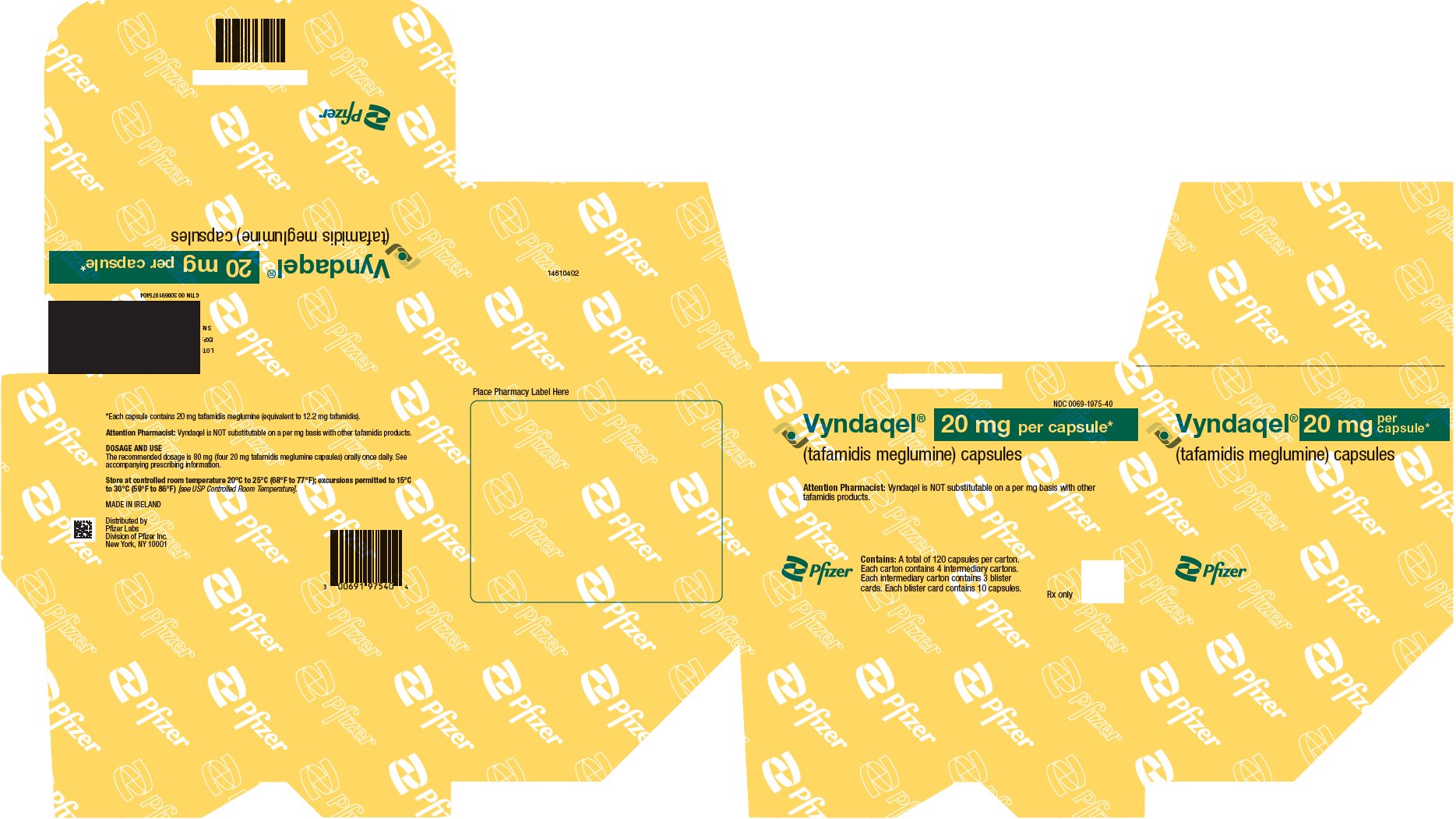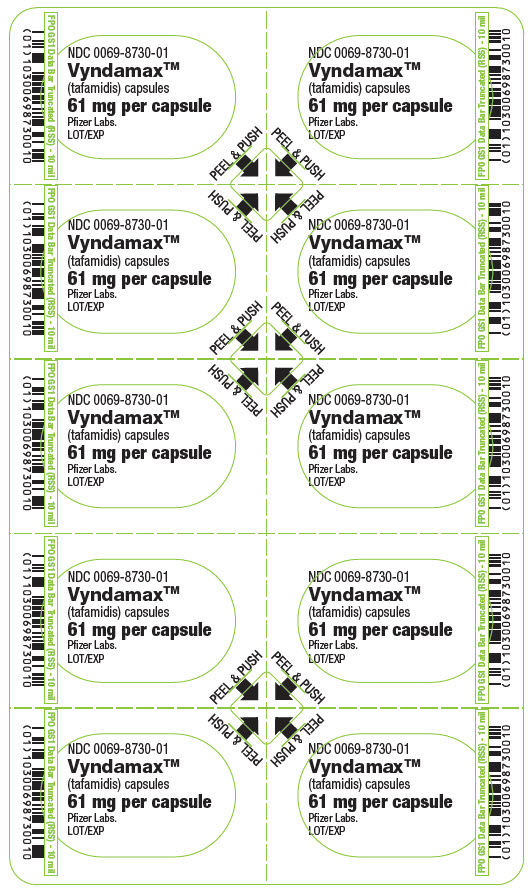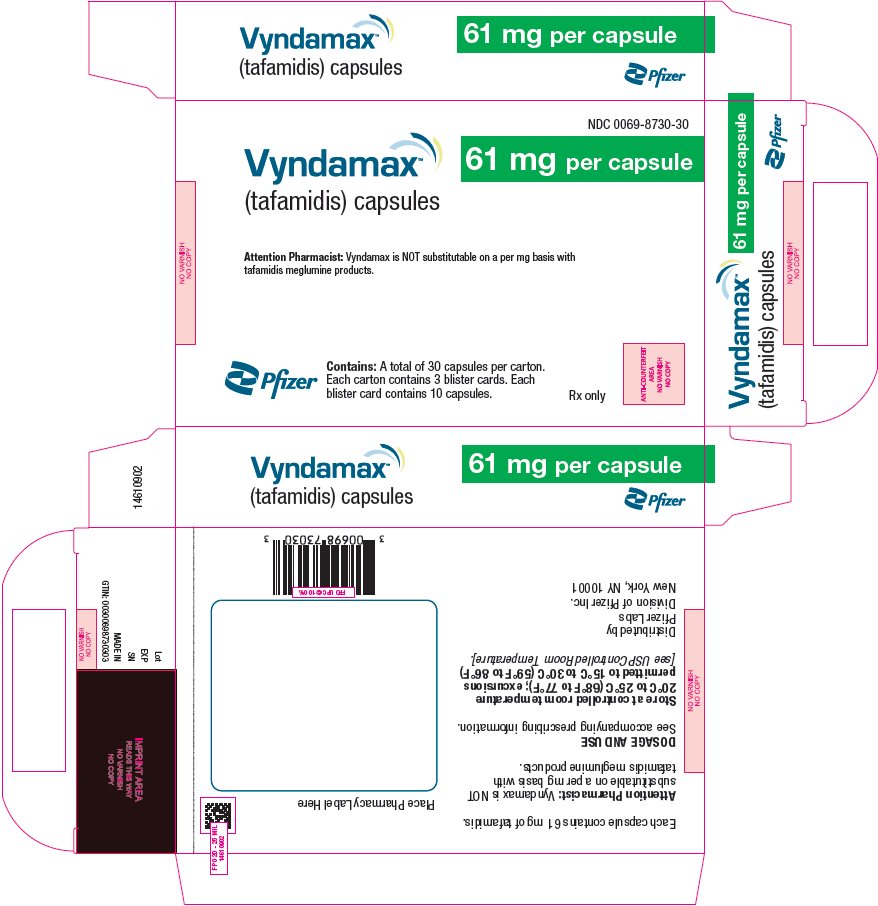 DRUG LABEL: Vyndaqel
NDC: 0069-1975 | Form: CAPSULE, LIQUID FILLED
Manufacturer: Pfizer Laboratories Div Pfizer Inc
Category: prescription | Type: HUMAN PRESCRIPTION DRUG LABEL
Date: 20250101

ACTIVE INGREDIENTS: TAFAMIDIS MEGLUMINE 20 mg/1 1
INACTIVE INGREDIENTS: AMMONIA; FD&C BLUE NO. 1; PIGMENT RED 48; GELATIN, UNSPECIFIED; GLYCERIN; FERRIC OXIDE YELLOW; POLYETHYLENE GLYCOL 400; POLYSORBATE 80; POLYVINYL ACETATE PHTHALATE; PROPYLENE GLYCOL; SORBITAN MONOOLEATE; SORBITOL; TITANIUM DIOXIDE

HIGHLIGHTS OF PRESCRIBING INFORMATION

These highlights do not include all the information needed to use VYNDAQEL and VYNDAMAX safely and effectively. See full prescribing information for VYNDAQEL and VYNDAMAX.
VYNDAQEL® (tafamidis meglumine) capsules, for oral administration
Initial U.S. Approval: 2019
VYNDAMAX™ (tafamidis) capsules, for oral administration
Initial U.S. Approval: 2019

1. INDICATIONS AND USAGE

VYNDAQEL and VYNDAMAX are transthyretin stabilizers indicated for the treatment of the cardiomyopathy of wild-type or hereditary transthyretin-mediated amyloidosis in adults to reduce cardiovascular mortality and cardiovascular-related hospitalization. (1)

2. DOSAGE AND ADMINISTRATION

The recommended dosage is either:

- VYNDAQEL 80 mg orally once daily, or
- VYNDAMAX 61 mg orally once daily (2.1)
- VYNDAMAX and VYNDAQEL are not substitutable on a per mg basis. (2.1)

3. DOSAGE FORMS AND STRENGTHS

Capsules: Tafamidis meglumine 20 mg and tafamidis 61 mg. (3)

4. CONTRAINDICATIONS

None. (4)

6. ADVERSE REACTIONS

To report SUSPECTED ADVERSE REACTIONS, contact Pfizer Inc. at 1-800-438-1985 or FDA at 1-800-FDA-1088 or www.fda.gov/medwatch.

8. USE IN SPECIFIC POPULATIONS

- Pregnancy: Based on animal studies, may cause fetal harm. (8.1)
- Lactation: Advise not to breastfeed. (8.2)

FULL PRESCRIBING INFORMATION

1. INDICATIONS AND USAGE

VYNDAQEL and VYNDAMAX are indicated for the treatment of the cardiomyopathy of wild-type or hereditary transthyretin-mediated amyloidosis (ATTR-CM) in adults to reduce cardiovascular mortality and cardiovascular-related hospitalization.

2. DOSAGE AND ADMINISTRATION

2.1 Recommended Dosage

The recommended dosage is either VYNDAQEL 80 mg (four 20-mg tafamidis meglumine capsules) orally once daily or VYNDAMAX 61 mg (one 61-mg tafamidis capsule) orally once daily.

VYNDAMAX and VYNDAQEL are not substitutable on a per mg basis [see Clinical Pharmacology (12.3)].

2.2 Administration Instructions

The capsules should be swallowed whole and not crushed or cut.

If a dose is missed, instruct patients to take the dose as soon as remembered or to skip the missed dose and take the next dose at the regularly scheduled time. Do not double the dose.

3. DOSAGE FORMS AND STRENGTHS

VYNDAQEL is available as:

- tafamidis meglumine 20 mg: yellow, opaque, oblong capsule, printed with "VYN 20" in red.

VYNDAMAX is available as:

- tafamidis 61 mg: reddish brown, opaque, oblong capsule, printed with "VYN 61" in white.

4. CONTRAINDICATIONS

None.

6. ADVERSE REACTIONS

6.1 Clinical Trials Experience

Because clinical trials are conducted under widely varying conditions, adverse reaction rates observed in the clinical trials of a drug cannot be directly compared to rates in the clinical trials of another drug and may not reflect the rates observed in practice.

The data reflect exposure of 377 ATTR-CM patients to 20 mg or 80 mg (administered as four 20-mg capsules) of VYNDAQEL administered daily for an average of 24.5 months (ranging from 1 day to 111 months).

Adverse events were assessed from ATTR-CM clinical trials with VYNDAQEL, primarily a 30-month placebo-controlled trial [see Clinical Studies (14)]. The frequency of adverse events in patients treated with VYNDAQEL 20 mg (n=88) or 80 mg (n=176; administered as four 20-mg capsules) was similar to that with placebo (n=177).

In the 30-month placebo-controlled trial, similar proportions of VYNDAQEL-treated patients and placebo-treated patients discontinued the study drug because of an adverse event: 12 (7%), 5 (6%), and 11 (6%) from the VYNDAQEL 80-mg, VYNDAQEL 20-mg, and placebo groups, respectively.

7. DRUG INTERACTIONS

7.1 BCRP Substrates

Tafamidis inhibits breast cancer resistant protein (BCRP) in humans [see Clinical Pharmacology (12.3)]. Coadministration of tafamidis and drugs that are BCRP substrates may increase the exposure of substrates of this transporter (e.g., methotrexate, rosuvastatin, imatinib) and the risk of the substrate-related toxicities. Monitor for signs of BCRP substrate-related toxicities and modify dosage of the substrate if appropriate.

8. USE IN SPECIFIC POPULATIONS

8.1 Pregnancy

Risk Summary

Based on findings from animal studies, VYNDAQEL and VYNDAMAX may cause fetal harm when administered to a pregnant woman. However, limited available human data with VYNDAQEL use in pregnant women (at a dose of 20 mg per day) have not identified any drug-associated risks for major birth defects, miscarriage, or adverse maternal or fetal outcomes. In animal reproductive studies, oral administration of tafamidis meglumine to pregnant rabbits during organogenesis resulted in adverse effects on development (embryofetal mortality, fetal body weight reduction and fetal malformation) at a dosage providing approximately 9 times the human exposure (AUC) at the maximum recommended human dose (MRHD) of VYNDAQEL (80 mg), and increased incidence of fetal skeletal variation at a dosage providing equivalent human exposure (AUC) at the MRHD. Postnatal mortality, growth retardation, and impaired learning and memory were observed in offspring of pregnant rats administered tafamidis meglumine during gestation and lactation at a dosage approximately 2 times the MRHD based on body surface area (mg/m^2) (see Data). Advise pregnant women of the potential risk to a fetus. Report pregnancies to the Pfizer reporting line at 1-800-438-1985.

The estimated background risk of major birth defects and miscarriage for the indicated population is unknown. All pregnancies have a background risk of birth defects, loss, or other adverse outcomes. In the U.S. general population, the estimated background risk of major birth defects and miscarriage in clinically recognized pregnancies is 2% to 4% and 15% to 20%, respectively.

Data

Animal Data

In pregnant rats, oral administration of tafamidis meglumine (0, 15, 30, and 45 mg/kg/day) throughout organogenesis resulted in decreased fetal body weights at ≥30 mg/kg/day (approximately 10 times the human exposure at the MRHD based on AUC). The no-observed-adverse-effect-level (NOAEL) for embryofetal development in rats was 15 mg/kg/day (approximately 7 times the human exposure at the MRHD based on AUC).

In pregnant rabbits, oral administration of tafamidis meglumine (0, 0.5, 2, and 8 mg/kg/day) throughout organogenesis resulted in increased embryofetal mortality, reduced fetal body weights, and an increased incidence of fetal malformations at 8 mg/kg/day (approximately 9 times the human exposure at the MRHD based on AUC), which was also maternally toxic. Increased incidences of fetal skeletal variations were observed at doses ≥0.5 mg/kg/day (approximately equivalent to the human exposure at the MRHD based on AUC).

In the pre- and postnatal study, pregnant rats received oral administration of tafamidis meglumine at doses of 0, 5, 15, or 30 mg/kg/day throughout pregnancy and lactation (Gestation Day 7 to Lactation Day 20). Decreased survival and body weights, delayed male sexual maturation and neurobehavioral effects (learning and memory impairment) were observed in the offspring of dams treated at 15 mg/kg/day (approximately 2 times the MRHD on a mg/m^2 basis). The NOAEL for pre- and postnatal development in rats was 5 mg/kg/day (approximately equivalent to the MRHD on a mg/m^2 basis).

8.2 Lactation

Risk Summary

There are no available data on the presence of tafamidis in human milk, the effect on the breastfed infant, or the effect on milk production. Tafamidis is present in rat milk (see Data). When a drug is present in animal milk, it is likely the drug will be present in human milk. Based on findings from animal studies which suggest the potential for serious adverse reactions in the breastfed infant, advise patients that breastfeeding is not recommended during treatment with VYNDAQEL or VYNDAMAX.

Data

Pregnant and lactating female rats were administered repeated daily oral doses of tafamidis meglumine (15 mg/kg/day) followed by a single oral gavage dose of ^14C-tafamidis meglumine on Lactation Day 4 or 12. Radioactivity was observed in milk by 1 hour post-dose and increased thereafter. The ratio of the highest radioactivity associated with ^14C tafamidis meglumine in milk (8 hours post-dose) vs. plasma (1 hour post-dose) was approximately 1.6 on Day 12, indicating tafamidis meglumine is transferred to milk after oral administration.

8.3 Females and Males of Reproductive Potential

Contraception

Females

Based on findings from animal studies, VYNDAQEL and VYNDAMAX may cause fetal harm when administered to a pregnant woman [see Use in Specific Populations (8.1)]. Consider pregnancy planning and prevention for females of reproductive potential.

8.4 Pediatric Use

The safety and effectiveness of VYNDAQEL and VYNDAMAX have not been established in pediatric patients.

8.5 Geriatric Use

No dosage adjustment is required for elderly patients (≥65 years) [see Clinical Pharmacology (12.3)]. Of the total number of patients in the clinical study (n=441), 90.5% were 65 and over, with a median age of 75 years.

10. OVERDOSAGE

There is minimal clinical experience with overdose. During clinical trials, two patients accidentally ingested a single VYNDAQEL dose of 160 mg without adverse events. The highest dose of tafamidis meglumine given to healthy volunteers in a clinical trial was 480 mg as a single dose. There was one reported adverse event of mild hordeolum at this dose.

11. DESCRIPTION

VYNDAQEL (tafamidis meglumine) and VYNDAMAX (tafamidis) contain tafamidis as the active moiety, which is a selective stabilizer of transthyretin.

The chemical name of tafamidis meglumine is 2-(3,5-dichlorophenyl)-1,3-benzoxazole-6-carboxylic acid mono (1-deoxy-1-methylamino-D-glucitol). The molecular formula is C14H7Cl2NO3 C7H17NO5, and the molecular weight is 503.33 g/mol. The structural formula is:

Tafamidis meglumine 20-mg soft gelatin capsule for oral use contains a white to pink colored suspension of tafamidis meglumine 20 mg (equivalent to 12.2 mg of tafamidis free acid), and the following inactive ingredients: ammonium hydroxide 28%, brilliant blue FCF, carmine, gelatin, glycerin, iron oxide (yellow), polyethylene glycol 400, polysorbate 80, polyvinyl acetate phthalate, propylene glycol, sorbitan monooleate, sorbitol, and titanium dioxide.

The chemical name of tafamidis is 2-(3,5-dichlorophenyl)-1,3-benzoxazole-6-carboxylic acid. The molecular formula is C14H7Cl2NO3, and the molecular weight is 308.12 g/mol. The structural formula is:

Tafamidis 61-mg soft gelatin capsule for oral use contains a white to pink colored suspension of tafamidis 61 mg and the following inactive ingredients: ammonium hydroxide 28%, butylated hydroxytoluene, gelatin, glycerin, iron oxide (red), polyethylene glycol 400, polysorbate 20, povidone (K-value 90), polyvinyl acetate phthalate, propylene glycol, sorbitol, and titanium dioxide.

12. CLINICAL PHARMACOLOGY

12.1 Mechanism of Action

Tafamidis is a selective stabilizer of TTR. Tafamidis binds to TTR at the thyroxine binding sites, stabilizing the tetramer and slowing dissociation into monomers, the rate-limiting step in the amyloidogenic process.

12.2 Pharmacodynamics

A proprietary TTR stabilization assay was utilized as a pharmacodynamic marker and assessed the stability of the TTR tetramer ex vivo. The TTR stabilization assay quantifies immunoturbidimetric measurement of the stable TTR tetramer in plasma pre- and post-treatment with 2-day in vitro denaturation with urea. Using this proprietary assay, a dose-dependent trend for greater TTR tetramer stabilization is observed for VYNDAQEL 80-mg compared to VYNDAQEL 20-mg. However, the clinical relevance of a higher TTR tetramer stabilization towards cardiovascular outcomes is not known.

VYNDAQEL stabilized both the wild-type TTR tetramer and the tetramers of 14 TTR variants tested clinically after once-daily dosing. Tafamidis also stabilized the TTR tetramer for 25 variants tested ex vivo.

VYNDAQEL and VYNDAMAX may decrease serum concentrations of total thyroxine, without an accompanying change in thyroid stimulating hormone (TSH). This reduction in total thyroxine values is probably the result of reduced thyroxine binding to or displacement from transthyretin (TTR) due to the high binding affinity of tafamidis to the TTR thyroxine receptor. No corresponding clinical findings consistent with hypothyroidism have been observed.

Biomarkers associated with heart failure (NT-proBNP and Troponin I) favored VYNDAQEL over placebo.

Cardiac Electrophysiology

At approximately 2.2 times the steady state peak plasma concentration (Cmax) at the recommended dose, tafamidis does not prolong the QTc interval to any clinically relevant extent.

12.3 Pharmacokinetics

No clinically significant differences in steady state Cmax and area under the plasma concentration over time curve (AUC) of tafamidis were observed for VYNDAMAX 61-mg capsule compared to VYNDAQEL administered as four 20-mg capsules.

Tafamidis exposure increases proportionally over single (up to 480 mg) or multiple (up to 80 mg) (1 to 6 times the approved recommended dosage) once daily dosing.

The apparent clearance were similar after single and repeated administration of VYNDAQEL 80 mg.

Absorption

Median tafamidis peak concentrations occurred within 4 hours following dosing.

Effect of Food

No clinically significant differences in the pharmacokinetics of tafamidis were observed following administration of a high fat, high calorie meal.

Distribution

The apparent steady state volume of distribution of tafamidis meglumine is 16 liters and 18.5 liters for tafamidis. Plasma protein binding of tafamidis is >99% in vitro. Tafamidis primarily binds to TTR.

Elimination

The mean half-life of tafamidis is approximately 49 hours. The apparent oral clearance of tafamidis meglumine is 0.228 L/h (0.263 L/h for tafamidis). The degree of drug accumulation at steady state after repeated tafamidis daily dosing is approximately 2.5-fold greater than that observed after a single dose.

Metabolism

The metabolism of tafamidis has not been fully characterized. However, glucuronidation has been observed.

Excretion

After a single oral dose of tafamidis meglumine 20 mg, approximately 59% of the dose was recovered in feces (mostly as the unchanged drug) and approximately 22% of the dose was recovered in urine (mostly as the glucuronide metabolite).

Specific Populations

No clinically significant differences in the pharmacokinetics of tafamidis were observed based on age, race/ethnicity (Caucasian and Japanese) or renal impairment.

Patients with Hepatic Impairment

Patients with moderate hepatic impairment (Child-Pugh Score of 7 to 9) had decreased systemic exposure (approximately 40%) and increased clearance (approximately 68%) of tafamidis compared to healthy subjects. As TTR levels are lower in subjects with moderate hepatic impairment than in healthy subjects, the exposure of tafamidis relative to the amount of TTR is sufficient to maintain stabilization of the TTR tetramer in these patients. No clinically significant differences in the pharmacokinetics of tafamidis were observed in patients with mild hepatic impairment (Child Pugh Score of 5 to 6) compared to healthy subjects. The effect of severe hepatic impairment on tafamidis is unknown.

Drug Interaction Studies

Clinical Studies

CYP3A4 substrates: No clinically significant differences in the pharmacokinetics of midazolam (a CYP3A4 substrate) or on the formation of its active metabolite (1-hydroxymidazolam) were observed when a single 7.5-mg dose of midazolam was administered prior to and after a 14-day regimen of VYNDAQEL 20-mg once daily.

BCRP substrates: Tafamidis inhibits breast cancer resistant protein (BCRP). In a clinical study in healthy participants, AUCinf and Cmax of the BCRP substrate rosuvastatin increased by 96.75% and 85.59%, respectively following multiple doses of VYNDAMAX 61 mg daily dosing.

In Vitro Studies

Cytochrome P450 Enzymes: Tafamidis induces CYP2B6 and CYP3A4 and does not induce CYP1A2. Tafamidis does not inhibit CYP1A2, CYP2B6, CYP2C8, CYP2C9, CYP2C19, CYP3A4/5 or CYP2D6.

UDP glucuronosyltransferase (UGT): Tafamidis inhibits intestinal activities of UGT1A1 but neither induces nor inhibits other UDP glucuronosyltransferase (UGT) systemically.

Transporter Systems: In vitro studies and model predictions show that tafamidis has a low potential to inhibit organic anion transporters OAT1 and OAT3 at clinically relevant concentrations. Tafamidis did not show a potential to inhibit Multi-Drug Resistant Protein (MDR1) (also known as P-glycoprotein; P-gp), organic cation transporter OCT2, multidrug and toxin extrusion transporters MATE1 and MATE2K and, organic anion transporting polypeptide OATP1B1 and OATP1B3.

13. NONCLINICAL TOXICOLOGY

13.1 Carcinogenesis, Mutagenesis, Impairment of Fertility

Carcinogenesis

There was no evidence of an increased incidence of neoplasia in the transgenic (Tg)-rasH2 mouse following repeated daily administration for 26 weeks at daily doses of 0, 10, 30 or 90 mg/kg. There was no evidence of increased incidence of neoplasia in a 2-year carcinogenicity study in rats at exposures up to 18 times the AUC at the MRHD.

Mutagenesis

There was no evidence of mutagenicity or clastogenicity in vitro, and an in vivo rat micronucleus study was negative.

Impairment of Fertility

There were no effects of tafamidis meglumine on fertility, reproductive performance, or mating behavior in the rat at any dose. Rats were dosed daily (0, 5, 15, and 30 mg/kg/day) prior to cohabitation (for at least 15 days for females and 28 days for males), throughout the cohabitation period to the day prior to termination of males and through to implantation of females (Gestation Day 7). No adverse effects were noted on male and female rats in toxicity, fertility, and mating behavior at any dose. The paternal and maternal no observed adverse effect level for reproductive toxicity of tafamidis meglumine is 30 mg/kg/day, approximately 4 times the MRHD on a mg/m^2 basis.

14. CLINICAL STUDIES

Efficacy was demonstrated in a multicenter, international, randomized, double-blind, placebo-controlled study in 441 patients with wild-type or hereditary ATTR-CM (NCT01994889).

Patients were randomized in a 1:2:2 ratio to receive VYNDAQEL 20 mg (n=88), VYNDAQEL 80 mg (administered as four 20-mg VYNDAQEL capsules) (n=176), or matching placebo (n=177) once daily for 30 months, in addition to standard of care (e.g., diuretics). Treatment assignment was stratified by the presence or absence of a variant TTR genotype as well as baseline disease severity (NYHA Class). Transplant patients were excluded from this study. Table 1 describes the patient demographics and baseline characteristics.

Table 1: Patient Demographics and Baseline Characteristics
Characteristic | Pooled Tafamidis N=264 | Placebo N=177
Age — years
Mean (standard deviation) | 74.5 (7.2) | 74.1 (6.7)
Median (minimum, maximum) | 75 (46, 88) | 74 (51, 89)
Sex — number (%)
Male | 241 (91.3) | 157 (88.7)
Female | 23 (8.7) | 20 (11.3)
TTR Genotype — number (%)
ATTRm | 63 (23.9) | 43 (24.3)
ATTRwt | 201 (76.1) | 134 (75.7)
NYHA Class — number (%)
NYHA Class I | 24 (9.1) | 13 (7.3)
NYHA Class II | 162 (61.4) | 101 (57.1)
NYHA Class III | 78 (29.5) | 63 (35.6)
Abbreviations: ATTRm = variant transthyretin amyloid, ATTRwt = wild-type transthyretin amyloid

The primary analysis used a hierarchical combination applying the method of Finkelstein-Schoenfeld (F-S) to all-cause mortality and frequency of cardiovascular-related hospitalizations, which was defined as the number of times a subject was hospitalized (i.e., admitted to a hospital) for cardiovascular-related morbidity. The method compared each patient to every other patient within each stratum in a pair-wise manner that proceeded in a hierarchical fashion using all-cause mortality followed by frequency of cardiovascular-related hospitalizations when patients could not be differentiated based on mortality.

This analysis demonstrated a significant reduction (p=0.0006) in all-cause mortality and frequency of cardiovascular-related hospitalizations in the pooled VYNDAQEL 20-mg and 80-mg groups versus placebo (Table 2).

Table 2: Primary Analysis Using Finkelstein-Schoenfeld (F-S) Method of All-Cause Mortality and Frequency of Cardiovascular-Related Hospitalizations
Primary Analysis | Pooled VYNDAQEL N=264 | Placebo N=177
Number (%) of Subjects Alive [Heart transplantation and cardiac mechanical assist device implantation are considered indicators of approaching end stage. As such, these subjects are treated in the analysis as equivalent to death. Therefore, such subjects are not included in the count of "Number of Subjects Alive at Month 30" even if such subjects are alive based on 30 month vital status follow-up assessment.] at Month 30 | 186 (70.5) | 101 (57.1)
Mean Number of Cardiovascular-related Hospitalizations During 30 months (per patient per year) Among Those Alive at Month 30 | 0.297 | 0.455
p-value from F-S Method | 0.0006

Analysis of the individual components of the primary analysis (all-cause mortality and cardiovascular-related hospitalization) also demonstrated significant reductions for VYNDAQEL versus placebo.

The hazard ratio from the all-cause mortality Cox-proportional hazard model for pooled VYNDAQEL versus placebo was 0.70 (95% confidence interval [CI] 0.51, 0.96), indicating a 30% relative reduction in the risk of death relative to the placebo group (p=0.026). Approximately 80% of total deaths were cardiovascular-related in both treatment groups. A Kaplan-Meier plot of time to event all-cause mortality is presented in Figure 1.

Figure 1: All-Cause Mortality [Heart transplants and cardiac mechanical assist devices treated as death. Hazard ratio from Cox proportional hazards model with treatment, TTR genotype (variant and wild-type), and NYHA baseline classification (NYHA Classes I and II combined and NYHA Class III) as factors.]

There were significantly fewer cardiovascular-related hospitalizations with VYNDAQEL compared with placebo with a reduction in risk of 32% corresponding to a Relative Risk Ratio of 0.68 (Table 3).

Table 3: Cardiovascular-Related Hospitalization Frequency
 | Pooled VYNDAQEL N=264 | Placebo N=177
Total (%) Number of Subjects with Cardiovascular-related Hospitalizations | 138 (52.3) | 107 (60.5)
Cardiovascular-related Hospitalizations per Year [This analysis was based on a Poisson regression model with treatment, TTR genotype (variant and wild-type), New York Heart Association (NYHA). Baseline classification (NYHA Classes I and II combined and NYHA Class III), treatment-by-TTR genotype interaction, and treatment-by-NYHA baseline classification interaction terms as factors.] | 0.48 | 0.70
Pooled VYNDAQEL vs Placebo Treatment Difference (Relative Risk Ratio) | 0.68
p-value | <0.0001

The treatment effects of VYNDAQEL on functional capacity and health status were assessed by the 6-Minute Walk Test (6MWT) and the Kansas City Cardiomyopathy Questionnaire-Overall Summary (KCCQ-OS) score, respectively. A significant treatment effect favoring VYNDAQEL was first observed at Month 6 and remained consistent through Month 30 on both 6MWT distance and KCCQ-OS score (Figure 2 and Table 4).

Figure 2: Change from Baseline to Month 30 in 6MWT Distance and KCCQ-OS Score

Abbreviations: 6MWT=6-Minute Walk Test, KCCQ-OS=Kansas City Cardiomyopathy Questionnaire-Overall Summary.

Panel A shows change from Baseline to Month 30 in pooled VYNDAQEL patients compared with placebo patients in 6MWT distance.

Panel B shows change from Baseline to Month 30 in pooled VYNDAQEL patients compared with placebo patients in KCCQ-OS score.

The Kansas City Cardiomyopathy Questionnaire-Overall Summary (KCCQ-OS) score is composed of four domains including Total Symptoms (Symptom Frequency and Symptom Burden), Physical Limitation, Quality of Life, and Social Limitation. The Overall Summary score and domain scores range from 0 to 100, with higher scores representing better health status. All four domains favored pooled VYNDAQEL compared to placebo at Month 30, and demonstrated similar treatment effects to the KCCQ-OS score (Figure 2 and Table 4). The distribution for change from Baseline to Month 30 for KCCQ-OS (Figure 3) shows that the proportion of patients with worse KCCQ-OS scores was lower for the pooled VYNDAQEL-treated group compared to placebo, and the proportion with improved scores was higher (Figure 3).

Figure 3: Histogram of Change from Baseline to Month 30 in KCCQ-Overall Summary Score

Abbreviation: KCCQ-OS=Kansas City Cardiomyopathy Questionnaire-Overall Summary.

Table 4: 6MWT Distance and KCCQ-OS Scores
Endpoints | Baseline Mean (SD) |  | Change from Baseline to Month 30, LS Mean (SE) |  | Treatment Difference from Placebo LS Mean (95% CI)
Endpoints | Pooled VYNDAQEL N=264 | Placebo N=177 | Pooled VYNDAQEL | Placebo | Treatment Difference from Placebo LS Mean (95% CI)
6MWT (meters) | 351 (121) | 353 (126) | -55 (5) | -131 (10) | 76 (58, 94)
KCCQ-OS | 67 (21) | 66 (22) | -7 (1) | -21 (2) | 14 (9, 18)
Abbreviations: 6MWT = 6-Minute Walk Test; KCCQ-OS = Kansas City Cardiomyopathy Questionnaire-Overall Summary; SD = standard deviation; LS = least squares; SE = standard error; CI = confidence interval

Results from the F-S method represented by win ratio for the combined endpoint and its components (all-cause mortality and frequency of CV-related hospitalization) consistently favored VYNDAQEL versus placebo across all subgroups (wild-type, variant and NYHA Class I & II, and III), except for CV-related hospitalization frequency in NYHA Class III (Figure 4). Win ratio is the number of pairs of VYNDAQEL-treated patient "wins" divided by number of pairs of placebo patient "wins." Analyses of 6MWT and KCCQ-OS also favored VYNDAQEL relative to placebo within each subgroup.

Figure 4: Results by Subgroup, Dose, and Components of Primary Analysis

Abbreviations: ATTRm = variant transthyretin amyloid, ATTRwt = wild-type transthyretin amyloid, F-S = Finkelstein Schoenfeld, CI = Confidence Interval

*F-S results presented using win ratio (based on all-cause mortality and frequency of cardiovascular hospitalization)

Heart transplants and cardiac mechanical assist devices treated as death.

Results of the primary analysis, 6MWT at Month 30 and KCCQ-OS at Month 30 were statistically significant for both the 80-mg and 20-mg doses of VYNDAQEL vs. placebo, with similar results for both doses.

16. HOW SUPPLIED/STORAGE AND HANDLING

VYNDAQEL 20-mg (tafamidis meglumine) soft gelatin capsules are yellow, opaque, oblong, and printed with "VYN 20" in red and supplied in the following package configurations:

VYNDAQEL Capsules
Package Configuration | Strength | NDC
Carton of 4 intermediary cartons. Each intermediary carton contains 3 blister cards. Each blister card contains 10 capsules. (120 total capsules) | 20 mg | NDC 0069-1975-40

VYNDAMAX 61-mg (tafamidis) soft gelatin capsules are reddish brown, opaque, oblong, and printed with "VYN 61" in white and supplied in the following package configurations:

VYNDAMAX Capsules
Package Configuration | Strength | NDC
Carton of 3 blister cards. Each blister card contains 10 capsules. (30 capsules total) | 61 mg | NDC 0069-8730-30

STORAGE AND HANDLING

Store VYNDAQEL and VYNDAMAX at controlled room temperature 20°C to 25°C (68°F to 77°F); excursions permitted to 15°C to 30°C (59°F to 86°F) [see USP Controlled Room Temperature].

17. PATIENT COUNSELING INFORMATION

Advise the patient to read the FDA-approved patient labeling (Patient Information).

Pregnancy

Report pregnancies to the Pfizer reporting line at 1-800-438-1985. Advise pregnant women and females of reproductive potential of the potential risk to a fetus. Advise females to inform their healthcare provider of a known or suspected pregnancy [see Use in Specific Populations (8.1)].

Lactation

Advise females not to breastfeed during treatment with VYNDAQEL or VYNDAMAX [see Use in Specific Populations (8.2)].

This product's label may have been updated. For full prescribing information, please visit www.pfizer.com.

For medical information about VYNDAQEL or VYNDAMAX, please visit www.pfizermedinfo.com or call 1‑800‑438‑1985.

LAB-0497-6.0

PATIENT INFORMATION

VYNDAQEL® (VIN-duh-kel)
(tafamidis meglumine)
capsules

VYNDAMAX™ (VIN-dah-max)
(tafamidis)
capsules

What is VYNDAQEL and VYNDAMAX?
VYNDAQEL and VYNDAMAX are prescription medicines used to treat adults with cardiomyopathy of wild-type or hereditary transthyretin-mediated amyloidosis (ATTR-CM) to reduce death and hospitalization related to heart problems.
It is not known if VYNDAQEL and VYNDAMAX are safe and effective in children.

Before taking VYNDAQEL or VYNDAMAX, tell your healthcare provider about all your medical conditions, including if you:

- have liver problems.
- are pregnant or plan to become pregnant. VYNDAQEL and VYNDAMAX may harm your unborn baby. Tell your healthcare provider right away if you become pregnant or think you may be pregnant during treatment with VYNDAQEL or VYNDAMAX. You may also report your pregnancy by calling the Pfizer reporting line at 1-800-438-1985.
- are breastfeeding or plan to breastfeed. It is not known if VYNDAQEL or VYNDAMAX passes into your breast milk. You should not breastfeed during treatment with VYNDAQEL or VYNDAMAX. Talk to your healthcare provider about the best way to feed your baby during treatment with VYNDAQEL or VYNDAMAX.

Tell your healthcare provider about all the medicines you take including any prescription or over-the-counter medicines, vitamins, and herbal supplements.

How should I take VYNDAQEL or VYNDAMAX?

- Take either VYNDAQEL or VYNDAMAX exactly as your healthcare provider tells you to.
- Take either VYNDAQEL or VYNDAMAX capsule(s) 1 time a day.
- VYNDAQEL or VYNDAMAX capsule(s) should be swallowed whole and not crushed or cut.
- If you miss a dose, take it as soon as you remember. If it is almost time for your next dose, skip the missed dose and take the next dose at your regularly scheduled time. Do not take 2 doses at the same time.

What are the possible side effects of VYNDAQEL and VYNDAMAX?
There were no known side effects that happened during treatment with VYNDAQEL or VYNDAMAX in people with cardiomyopathy of transthyretin-mediated amyloidosis.
You may report side effects to FDA at 1-800-FDA-1088.

How should I store VYNDAQEL and VYNDAMAX?

- Store VYNDAQEL and VYNDAMAX capsules at room temperature between 68°F to 77°F (20°C to 25°C).
- Keep VYNDAQEL and VYNDAMAX and all medicines out of the reach of children.

General information about the safe and effective use of VYNDAQEL and VYNDAMAX.
Medicines are sometimes prescribed for purposes other than those listed in a Patient Information leaflet. Do not use VYNDAQEL or VYNDAMAX for a condition for which it was not prescribed. Do not give VYNDAQEL or VYNDAMAX to other people, even if they have the same symptoms you have. It may harm them.
You can ask your healthcare provider or pharmacist for information about VYNDAQEL or VYNDAMAX that is written for healthcare professionals.

What are the ingredients in VYNDAQEL and VYNDAMAX?
VYNDAQEL:
Active ingredient: tafamidis meglumine
Inactive ingredients: ammonium hydroxide 28%, brilliant blue FCF, carmine, gelatin, glycerin, iron oxide (yellow), polyethylene glycol 400, polysorbate 80, polyvinyl acetate phthalate, propylene glycol, sorbitan monooleate, sorbitol, and titanium dioxide
VYNDAMAX:
Active ingredient: tafamidis
Inactive ingredients: ammonium hydroxide 28%, butylated hydroxytoluene, gelatin, glycerin, iron oxide (red), polyethylene glycol 400, polysorbate 20, povidone (K-value 90), polyvinyl acetate phthalate, propylene glycol, sorbitol, and titanium dioxide

LAB-0573-5.0
For more information, go to www.vyndaqel.com or call 1-800-438-1985.

This Patient Information has been approved by the U.S. Food and Drug Administration

Issued: 10/2023

PRINCIPAL DISPLAY PANEL - 20 mg Capsule Blister Card

NDC 0069-1975-12

Vyndaqel®
(tafamidis meglumine) capsules

20 mg per capsule

Pfizer Labs.
LOT/EXP

PEEL & PUSH

PRINCIPAL DISPLAY PANEL - 20 mg Capsule Blister Card Carton

Vyndaqel®
(tafamidis meglumine) capsules
20 mg per capsule*

Attention Pharmacist: Vyndaqel is NOT substitutable on a per mg basis
with other tafamidis products.

NOT FOR INDIVIDUAL RESALE

Pfizer
Contains: A total of 30 capsules per carton.
Each carton contains 3 blister cards. Each
blister card contains 10 capsules.

Rx only

PRINCIPAL DISPLAY PANEL - 20 mg Capsule Blister Card Carton Carton

NDC 0069-1975-40

Vyndaqel®
(tafamidis meglumine) capsules
20 mg per capsule*

Attention Pharmacist: Vyndaqel is NOT substitutable on a per mg basis with other
tafamidis products.

Pfizer
Contains: A total of 120 capsules per carton.
Each carton contains 4 intermediary cartons.
Each intermediary carton contains 3 blister
cards. Each blister card contains 10 capsules.

Rx only

PRINCIPAL DISPLAY PANEL - 61 mg Capsule Blister Card

NDC 0069-8730-01

Vyndamax™
(tafamidis) capsules

61 mg per capsule

Pfizer Labs.
LOT/EXP

PEEL & PUSH

PRINCIPAL DISPLAY PANEL - 61 mg Capsule Blister Card Carton

NDC 0069-8730-30

Vyndamax™
(tafamidis) capsules
61 mg per capsule

Attention Pharmacist: Vyndamax is NOT substitutable on a per mg basis with
tafamidis meglumine products.

Pfizer
Contains: A total of 30 capsules per carton.
Each carton contains 3 blister cards. Each
blister card contains 10 capsules.

Rx only